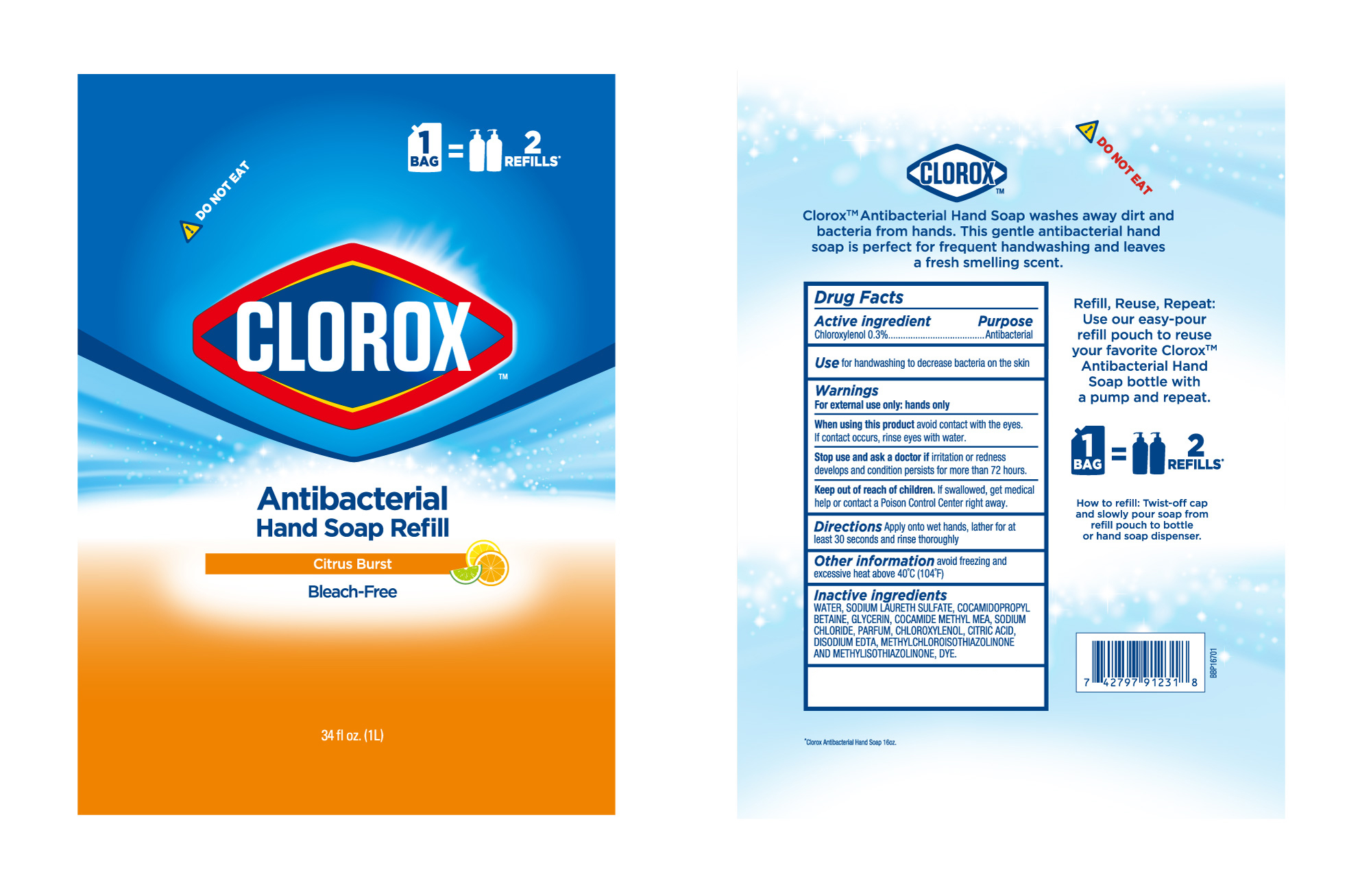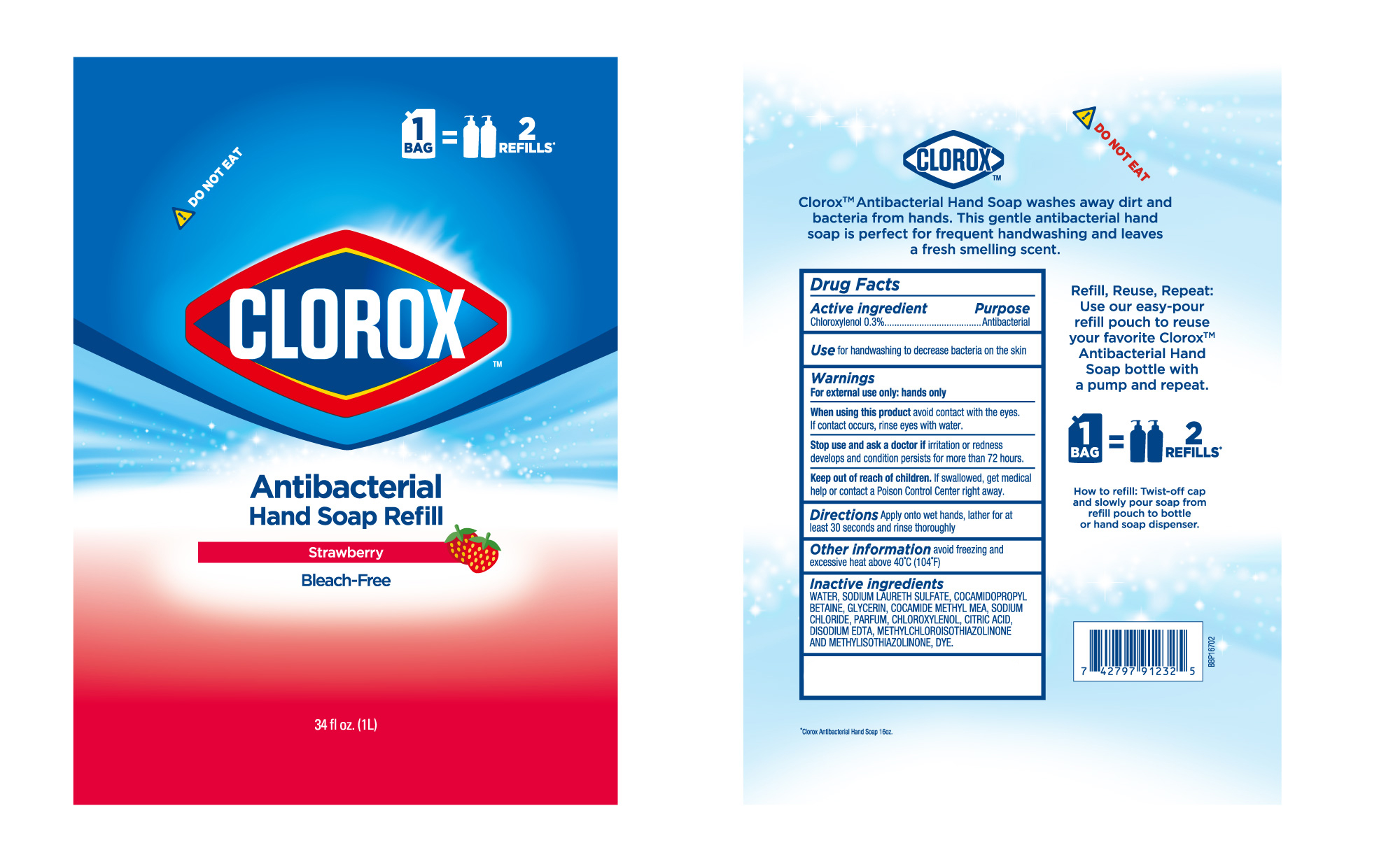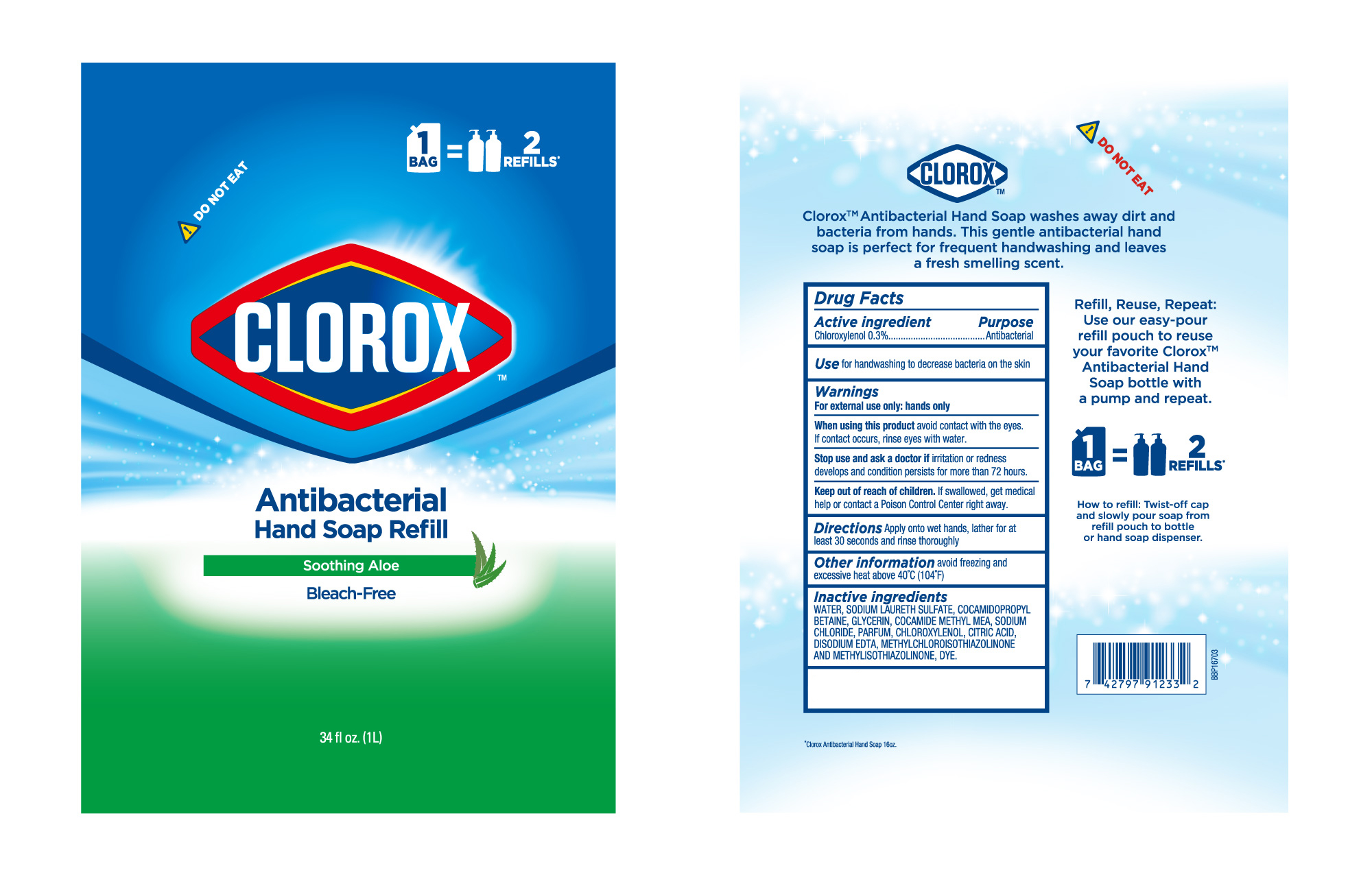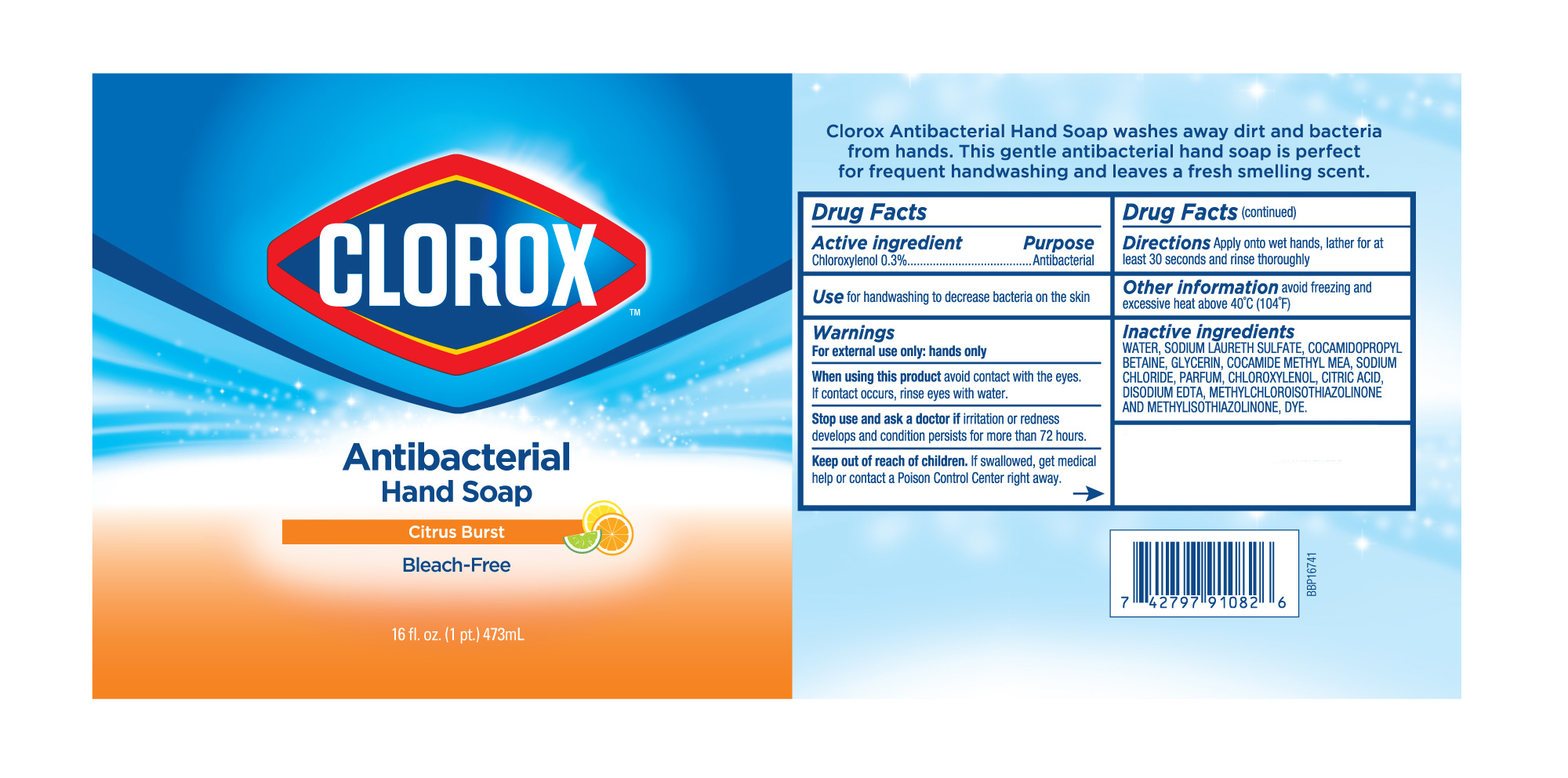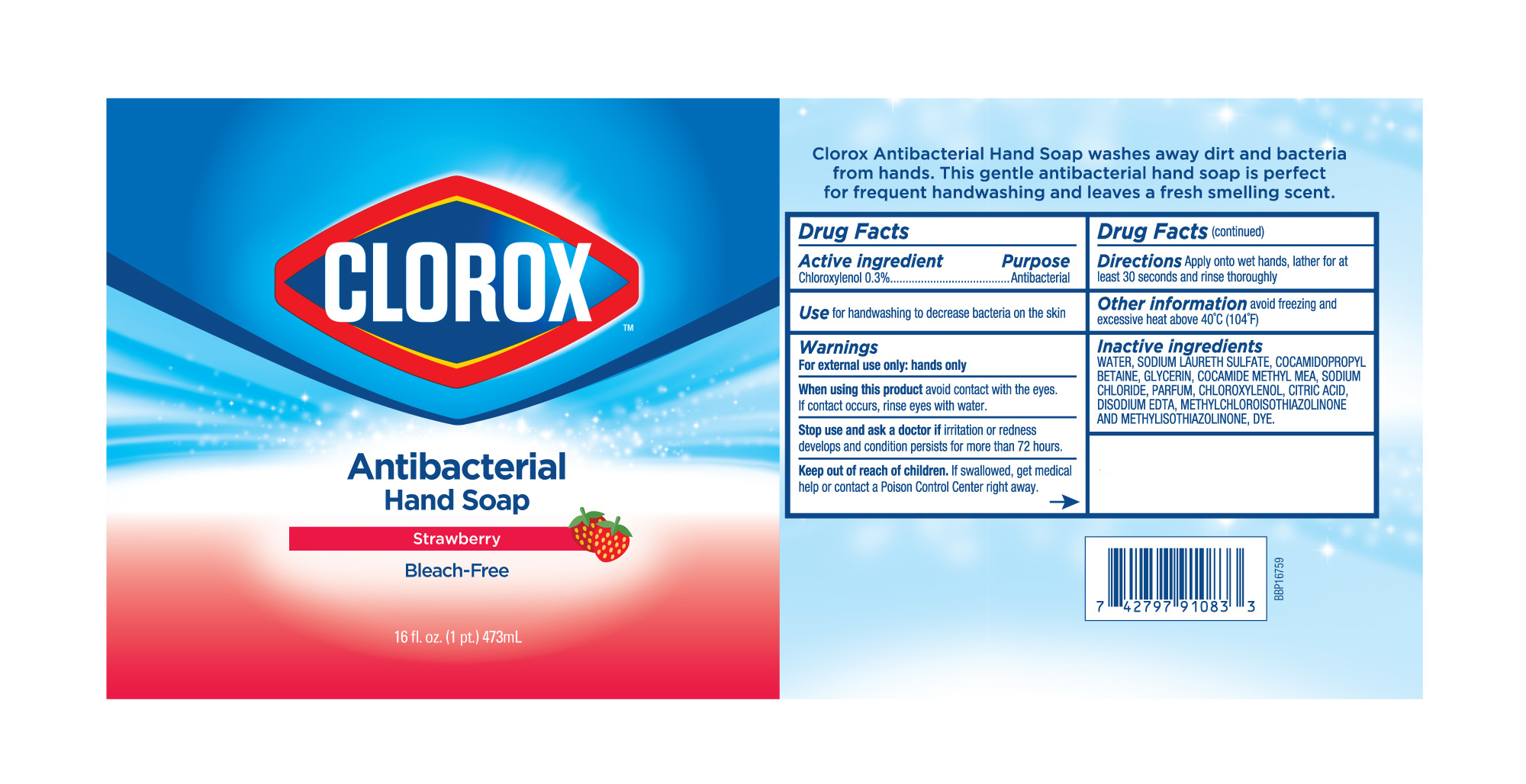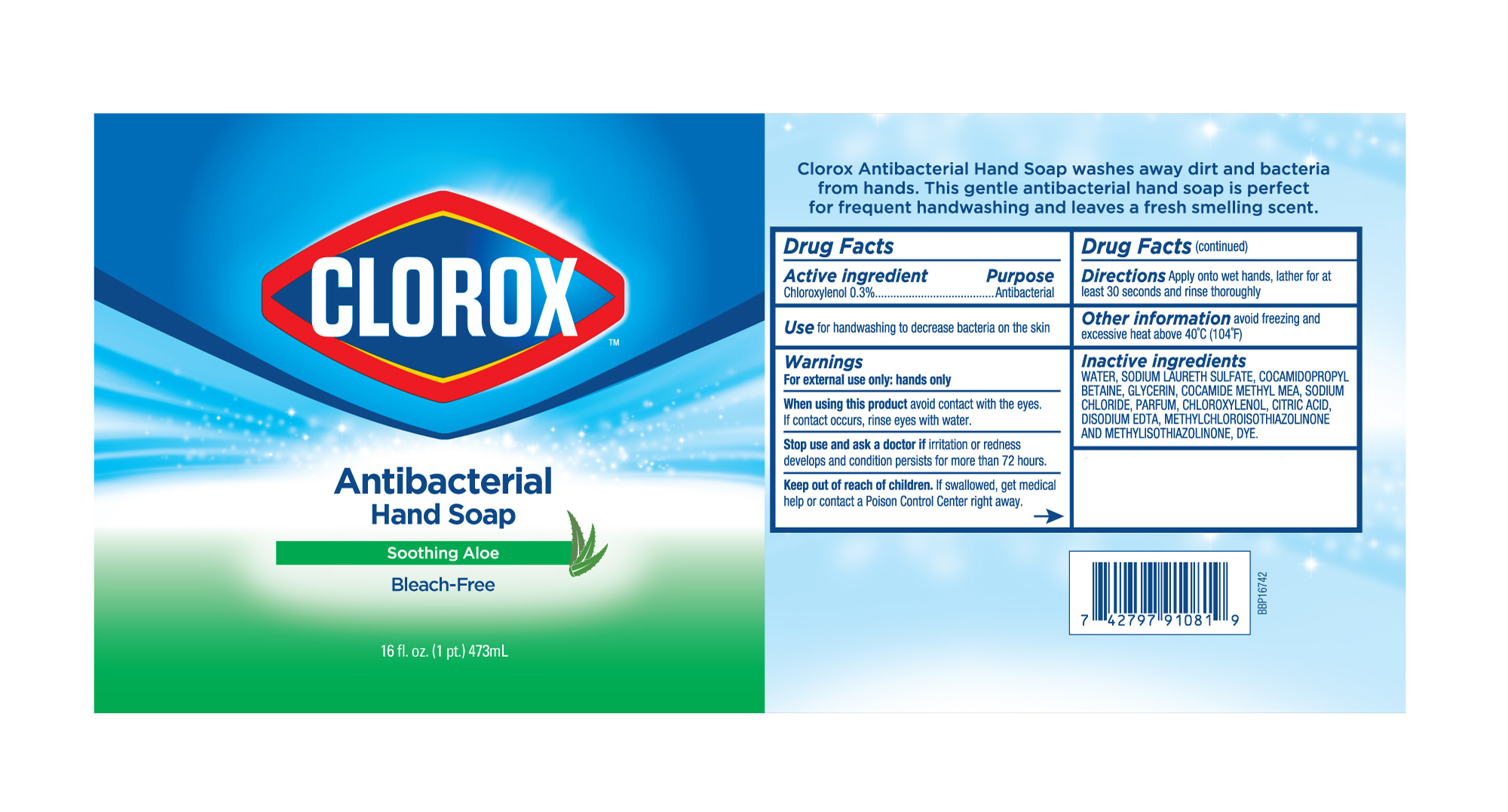 DRUG LABEL: HANDSOAP
NDC: 47993-326 | Form: GEL
Manufacturer: NINGBO JIANGBEI OCEAN STAR TRADING CO.,LTD
Category: otc | Type: HUMAN OTC DRUG LABEL
Date: 20210617

ACTIVE INGREDIENTS: CHLOROXYLENOL 0.3 g/100 mL
INACTIVE INGREDIENTS: WATER; SODIUM LAURETH SULFATE; COCAMIDOPROPYL BETAINE; GLYCERIN; COCOYL METHYL MONOETHANOLAMINE; SODIUM CHLORIDE; CITRIC ACID MONOHYDRATE; EDETATE DISODIUM; METHYLCHLOROISOTHIAZOLINONE/METHYLISOTHIAZOLINONE MIXTURE

47993-326

Active ingredients

Chloroxylenol 0.3%

PURPOSE

Antibacterial

INDICATIONS AND USAGE

Use for handwashing to decrease bacteria on the skin.

Warnings:

For external use only: hands only.

When using this product avoid contact with eyes. If contact occurs, rinse eyes with water.

Stop use and ask a doctor if irritation or redness develops and condition persists for more than 72 hours.

Keep out of reach of children. If swallowed, get medical help or contact a Poison Control Center right away.

Directions:

Apply onto wet hands, lather for at least 30 seconds and rinse thoroughly.

Other information:

Avoid freezing and excessive heat above 40℃ (104℉).

Inactive ingredients:

WATER, SODIUM LAURETH SULFATE, COCAMIDOPROPYL BETAINE, GLYCERIN, COCAMIDE METHYL MEA, SODIUM CHLORIDE, PARFUM, CHLOROXYLENOL, CITRIC ACID, DISODIUM EDTA, METHYLCHLOROISOTHIAZOLINONE AND METHYLISOTHIAZOLINONE, DYE